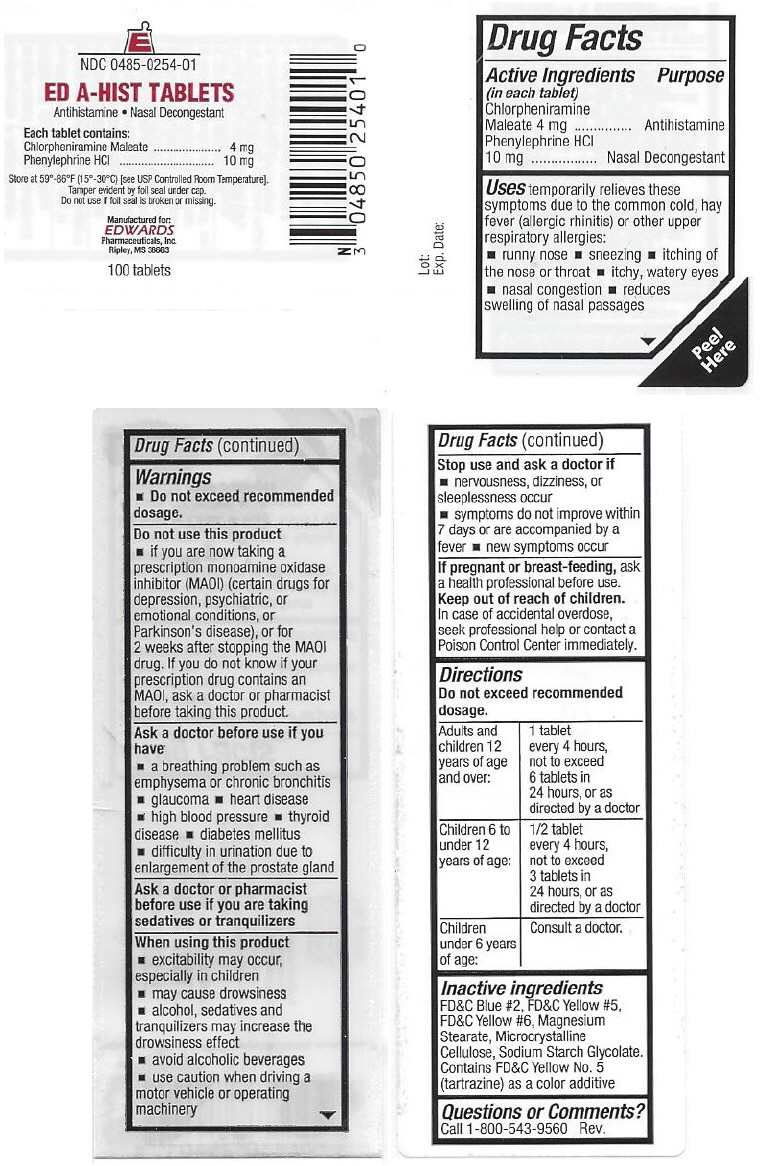 DRUG LABEL: ED A-HIST
NDC: 0485-0254 | Form: TABLET, COATED
Manufacturer: EDWARDS PHARMACEUTICALS, INC.
Category: otc | Type: HUMAN OTC DRUG LABEL
Date: 20241107

ACTIVE INGREDIENTS: CHLORPHENIRAMINE MALEATE 4 mg/1 1; PHENYLEPHRINE HYDROCHLORIDE 10 mg/1 1
INACTIVE INGREDIENTS: FD&C BLUE NO. 2; FD&C YELLOW NO. 5; FD&C YELLOW NO. 6; MAGNESIUM STEARATE; CELLULOSE, MICROCRYSTALLINE; SODIUM STARCH GLYCOLATE TYPE A CORN

ED A-HIST TABLETS

Drug Facts

ACTIVE INGREDIENT

Active Ingredients (in each tablet) | Purpose
Chlorpheniramine Maleate 4 mg | Antihistamine
Phenylephrine HCl 10 mg | Nasal Decongestant

Uses

temporarily relieves these symptoms due to the common cold, hay fever (allergic rhinitis) or other upper respiratory allergies:

- runny nose
- sneezing
- itching of the nose or throat
- itchy, watery eyes
- nasal congestion
- reduces swelling of nasal passages

Warnings

- Do not exceed recommended dosage.

Do not use this product

- if you are now taking a prescription monoamine oxidase inhibitor (MAOI) (certain drugs for depression, psychiatric, or emotional conditions, or Parkinson's disease), or for 2 weeks after stopping the MAOI drug. If you do not know if your prescription drug contains an MAOI, ask a doctor or pharmacist before taking this product.

Ask a doctor before use if you have

- a breathing problem such as emphysema or chronic bronchitis
- glaucoma
- heart disease
- high blood pressure
- thyroid disease
- diabetes mellitus
- difficulty in urination due to enlargement of the prostate gland

Ask a doctor or pharmacist before use if you are taking sedatives or tranquilizers

When using this product

- excitability may occur, especially in children
- may cause drowsiness
- alcohol, sedatives and tranquilizers may increase the drowsiness effect
- avoid alcoholic beverages
- use caution when driving a motor vehicle or operating machinery

Stop use and ask a doctor if

- nervousness, dizziness, or sleeplessness occur
- symptoms do not improve within 7 days or are accompanied by a fever
- new symptoms occur

PREGNANCY OR BREAST FEEDING

If pregnant or breast-feeding, ask a health professional before use.

Keep out of reach of children. In case of accidental overdose, seek professional help or contact a Poison Control Center immediately.

Directions

Do not exceed recommended dosage.

Adults and children 12 years of age and over: | 1 tablet every 4 hours, not to exceed 6 tablets in 24 hours, or as directed by a doctor
Children 6 to under 12 years of age: | 1/2 tablet every 4 hours, not to exceed 3 tablets is 24 hours, or as directed by a doctor
Children under 6 years of age: | Consult a doctor.

Inactive ingredients

FD&C Blue #2, FD&C Yellow #5, FD&C Yellow #6, Magnesium Stearate, Microcrystalline Cellulose, Sodium Starch Glycolate. Contains FD&C Yellow No. 5 (tartrazine) as a color additive

Questions or Comments?

Call 1-800-543-9560 Rev.

PRINCIPAL DISPLAY PANEL - 100 Tablet Bottle Label

NDC 0485-0254-01

ED A-HIST TABLETS

Antihistamine • Nasal Decongestant

Each tablet contains:
Chlorpheniramine Maleate 4 mg
Phenylephrine HCl 10 mg

Store at 59°-86°F (15°-30°C) [see USP Controlled Room Temperature].
Tamper evident by foil seal under cap.
Do not use if foil seal is broken or missing.

Manufactured for:
EDWARDS
Pharmaceuticals, Inc.
Ripley, MS 38663

100 tablets